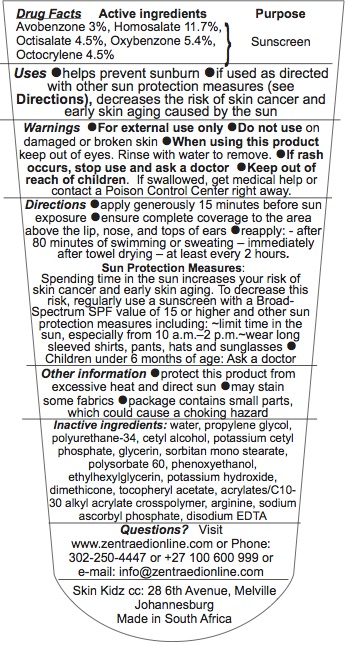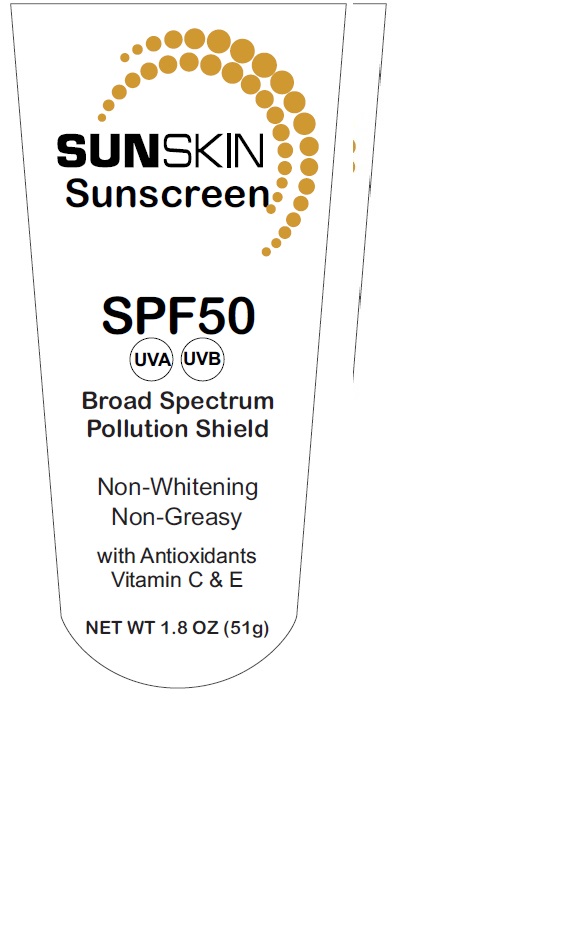 DRUG LABEL: Sunscreen
NDC: 72376-001 | Form: LOTION
Manufacturer: SKIN KIDZ CC
Category: otc | Type: HUMAN OTC DRUG LABEL
Date: 20180622

ACTIVE INGREDIENTS: Avobenzone 30 mg/1 g; HOMOSALATE 117 mg/1 g; OCTISALATE 45 mg/1 g; OXYBENZONE 54 mg/1 g; OCTOCRYLENE 45 mg/1 g
INACTIVE INGREDIENTS: Propylene glycol; Water; POLYURETHANE-34 (40 MPA, TENSILE STRENGTH OF FILM AT BREAK); Cetyl alcohol; Potassium cetyl phosphate; Glycerin; Sorbitan monostearate; Polysorbate 60; Phenoxyethanol; Ethylhexylglycerin; Potassium hydroxide; Dimethicone; .ALPHA.-TOCOPHEROL ACETATE; CARBOMER COPOLYMER TYPE B (ALLYL PENTAERYTHRITOL CROSSLINKED); Arginine; Sodium ascorbyl phosphate; EDETATE DISODIUM ANHYDROUS

Sun Skin SPF50 Sunscreen

PURPOSE

Sunscreen

Uses

● helps prevent sunburn

● if used as directed with other sun protection measures

- decreases the risk of skin cancer and early skin aging caused by the sun

Active ingredients

Avobenzone 3%, Homosalate 11.7%,
Octisalate 4.5%, Oxybenzone 5.4%,
Octocrylene 4.5%

Directions

● apply generously 15 minutes before sun exposure

● ensure complete coverage to the are above the lip, nose, and tops of ears

● reapply: - after 80 minutes of swimming or sweating – immediately after towel drying – at least every 2 hours.

WARNING AND Pracaution

●For external use only

●Do not use on damaged or broken skin

●When using this product keep out of eyes. Rinse with water to remove.

●If rash occurs, stop use and ask a doctor

ASK DOCTOR SECTION

●If rash occurs, stop use and ask a doctor

KEEP OUT OF REACH OF CHILDREN SECTION

- If swallowed, get medical help or contact a Poison Control Center right away.

INACTIVE INGREDIENT

ingredients: water, propylene glycol,
polyurethane-34, cetyl alcohol, potassium cetyl
phosphate, glycerin, sorbitan mono stearate,
polysorbate 60, phenoxyethanol,
ethylhexylglycerin, potassium hydroxide,
dimethicone, tocopheryl acetate, acrylates/C10-
30 alkyl acrylate crosspolymer, arginine, sodium
ascorbyl phosphate, disodium EDTA